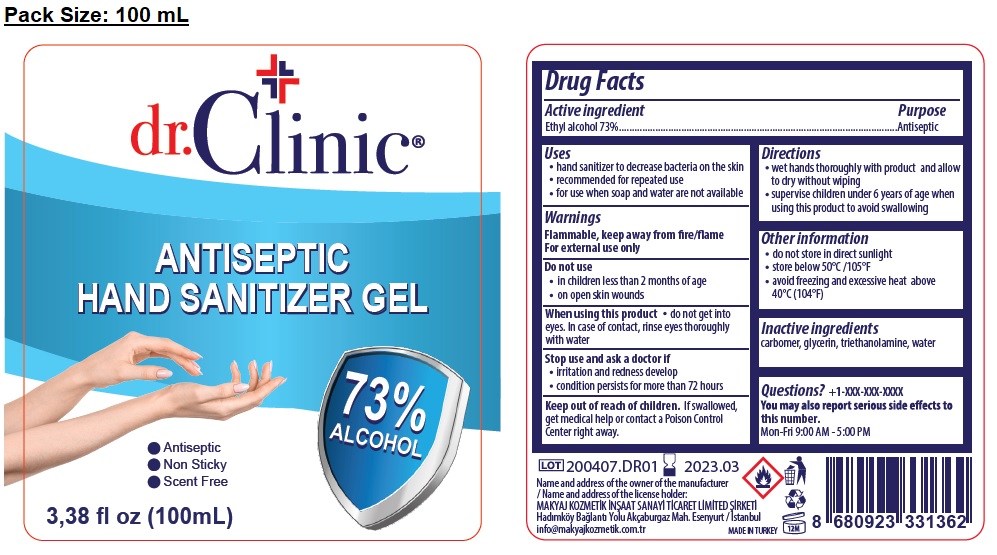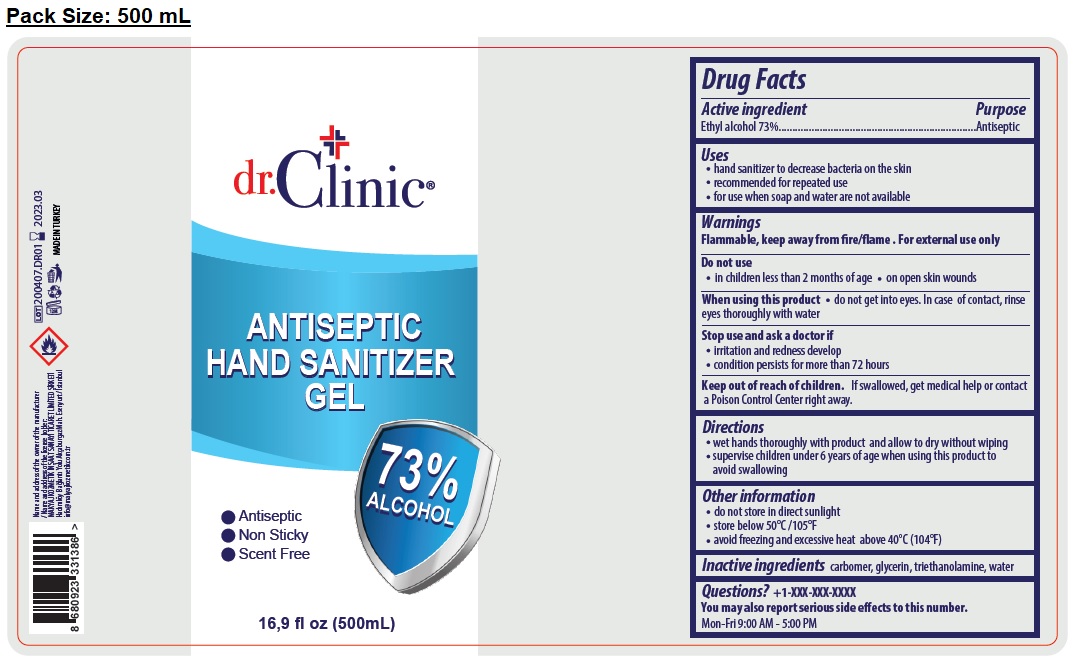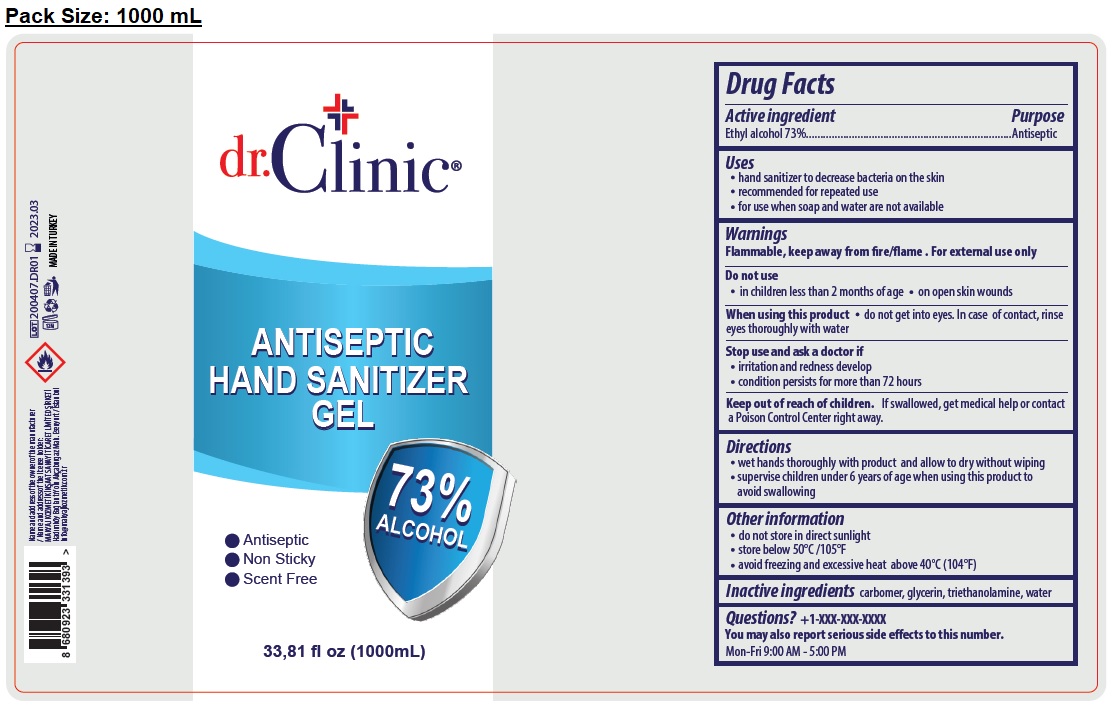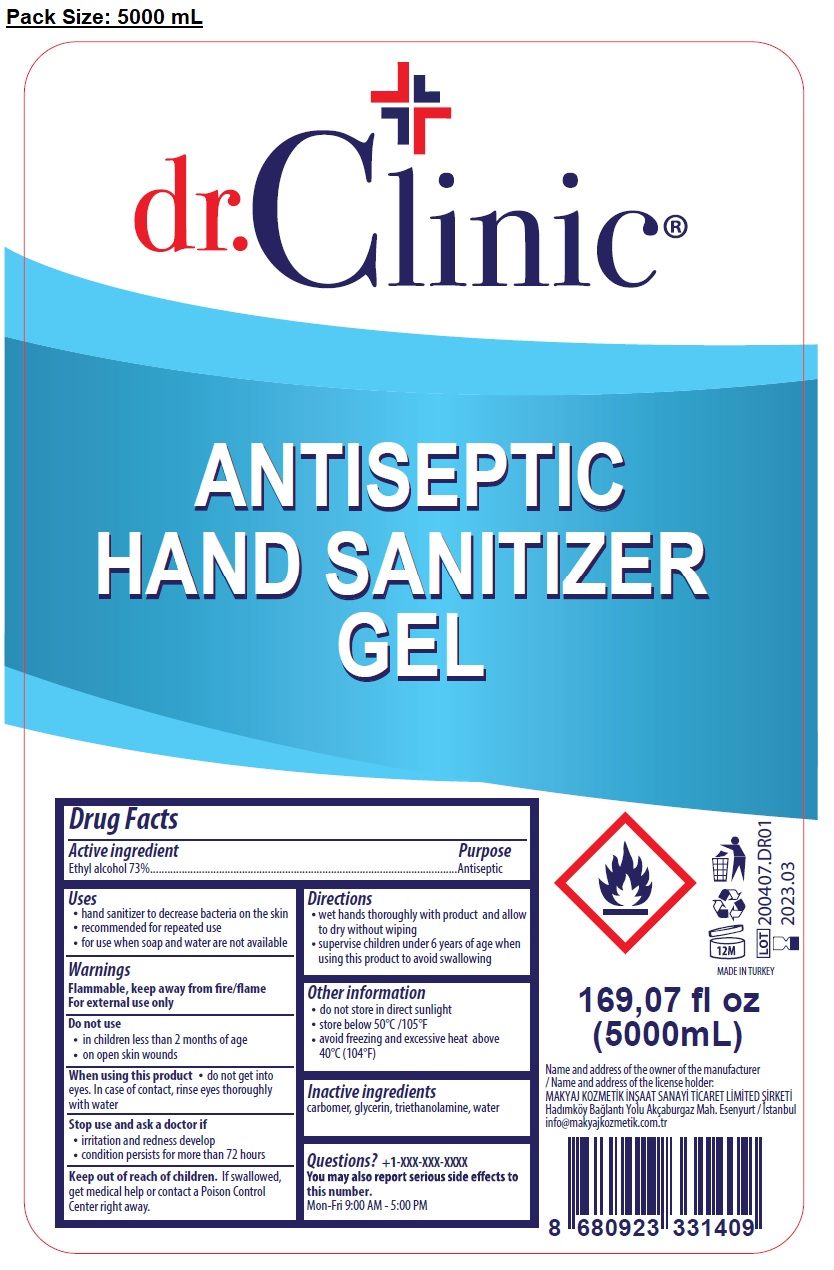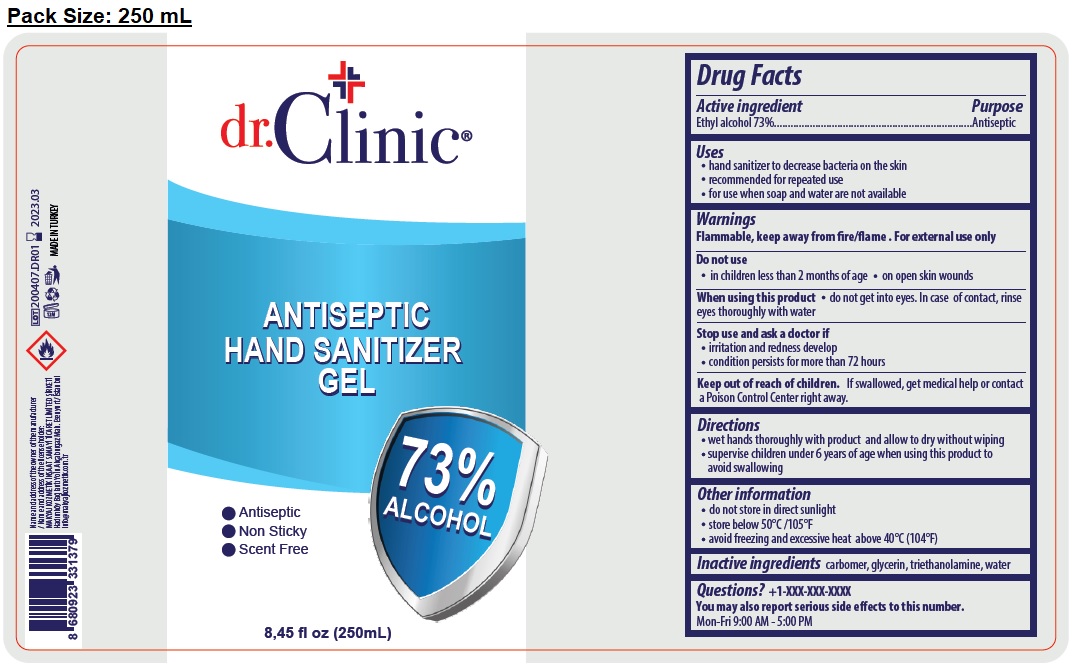 DRUG LABEL: DR.CLINIC ANTIBACTERIAL HAND SANITIZER
NDC: 76725-101 | Form: GEL
Manufacturer: MAKYAJ KOZMETIK INSAAT SANAYI VE TICARET LIMITED SIRKETI
Category: otc | Type: HUMAN OTC DRUG LABEL
Date: 20200730

ACTIVE INGREDIENTS: ALCOHOL 73 mL/100 mL
INACTIVE INGREDIENTS: CARBOMER HOMOPOLYMER, UNSPECIFIED TYPE; GLYCERIN; TROLAMINE; WATER

dr.Clinic® ANTIBACTERIAL HAND GEL

Active ingredient

Ethyl alcohol 73%

Purpose

Antibacterial

Uses

- hand sanitizer to decrease bacteria on the skin
- recommended for repeated use
- for use when soap and water are not available

Warnings

Flammable, keep away from fire/flame

For external use only

Do not use

• in children less than 2 months of age

• on open skin wounds

When using this product • do not get into eyes. In case of contact, rinse eyes thoroughly with water

Stop use and ask a doctor if

• irritation and redness develop

• condition persists for more than 72 hours

Keep out of reach of children. If swallowed, get medical help or contact a Poison Control Center right away.

Directions

- wet hands thoroughly with product and allow to dry without wiping
- supervise children under 6 years of age when using this product to avoid swallowing

Other information

- do not store in direct sunlight
- store below 50°C/105°F
- avoid freezing and excessive heat above 40°C (104°F)

Inactive ingredients

carbomer, glycerin, triethanolamine, water

Question? +1-XXX-XXX-XXXX

You may also report serious side effects to this number.

Mon-Fri 9.00 AM - 5.00 PM

MADE IN TURKEY

Name and address of the owner of the manufacturer

/ Name and address of the license holder:

MAKYAJ KOZMETIK IN‑AAT SANAYI TICARET LIMITED ‑IRKETI

Hadımköy Baglantı Yolu Akçaburgaz Mah. Esenyurt / Istanbul

info@makyajkozmetik.com.tr